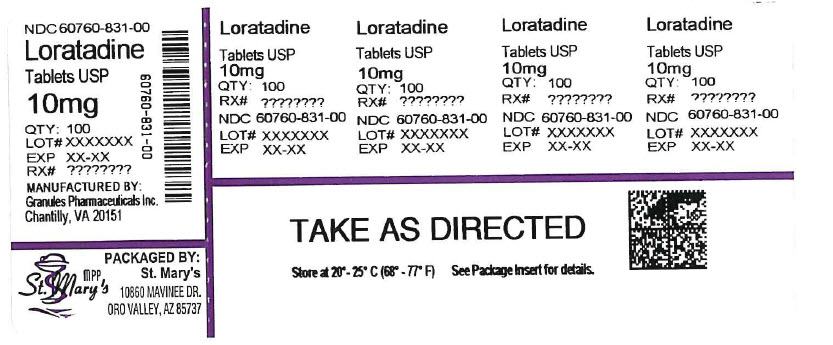 DRUG LABEL: Loratadine
NDC: 60760-831 | Form: TABLET
Manufacturer: ST. MARY'S MEDICAL PARK PHARMACY
Category: otc | Type: HUMAN OTC DRUG LABEL
Date: 20251208

ACTIVE INGREDIENTS: LORATADINE 10 mg/1 1
INACTIVE INGREDIENTS: LACTOSE MONOHYDRATE; STARCH, CORN; MAGNESIUM STEARATE; SODIUM STARCH GLYCOLATE TYPE A POTATO

Loratadine Tablets, 10 mg

ACTIVE INGREDIENT(S)

Loratadine 10 mg

PURPOSE

Antihistamine

USE(S)

temporarily relieves these symptoms due to hay fever or other upper respiratory allergies:
 runny nose

 sneezing
 itchy, water eyes
 itching of the nose or throat

WARNINGS

DO NOT USE

if you have ever had an allergic reaction to this product or any of its ingredients

ASK A DOCTOR BEFORE USE IF

you have liver or kidney disease. Your doctor should determine if you need a different dose.

WHEN USING THIS PRODUCT

do not take more than directed. Taking more than directed may cause drowsiness.

STOP USE AND ASK DOCTOR IF

an allergic reaction to this product occurs. Seek medical help right away.

PREGNANCY/BREASTFEEDING

ask a health professional before use

KEEP OUT OF REACH OF CHILDREN

In case of overdose, get medical help or contact a Poison Control Center right away.

DIRECTIONS

adults and children 6 years and over | 1 tablet daily; not more than 1 tablet in 24 hours
children under 6 years of age | ask a doctor
consumers with liver or kidney disease | ask a doctor

OTHER INFORMATION

Tamper-evident: do not use if foil seal under cap, printed with "SEALED for YOUR PROTECTION" is missing, open or broken

Blister Foil Units
safety sealed: do not use if the individual blister unit is open or torn

STORAGE

store between 20º to 25ºC (68º to 77ºF)

INACTIVE INGREDIENTS

Lactose monohydrate, magnesium stearate, sodium starch glycolate and starch maize pregelatinized

QUESTIONS OR COMMENTS

Contact 1-877-770-3183 Mon-Fri 9:00 AM to 4:30 PM EST.